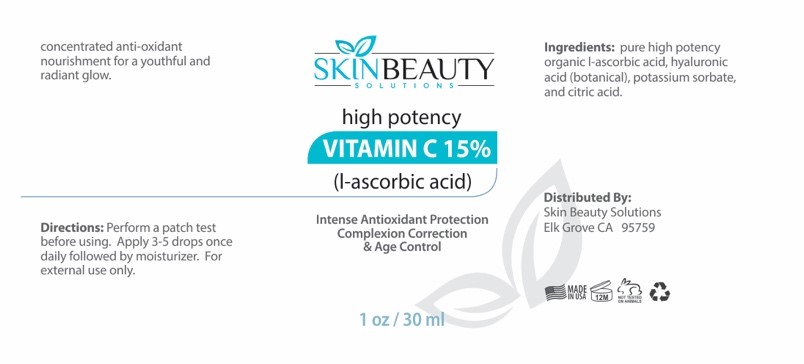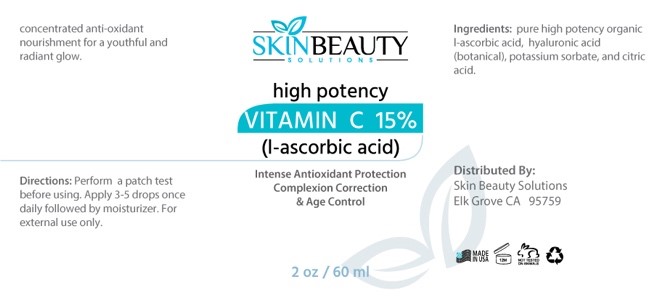 DRUG LABEL: Vitamin C  15% (L- Ascorbic Acid)
NDC: 84785-0053 | Form: SOLUTION
Manufacturer: Gazebo Wellness SKIN LLC
Category: otc | Type: HUMAN OTC DRUG LABEL
Date: 20241218

ACTIVE INGREDIENTS: ASCORBIC ACID 0.3 mg/30 mL; HYALURONIC ACID 0.3 mg/30 mL
INACTIVE INGREDIENTS: CITRIC ACID ACETATE; POTASSIUM SORBATE

DOSAGE AND ADMINISTRATION

Directions: Perform a patch test before using. Apply 3-5 drops once daily followed by moisturizer. For external use only.

WARNINGS

Directions: Perform a patch test before using. Apply 3-5 drops once daily followed by moisturizer. For external use only.

Inactive ingredients: Potassium Sorbate, Citric Acid.

Active ingredients: L-Ascorbic Acid, Hyaluronic Acid (Botanical).

PURPOSE

high potency VITAMIN C 15% (I-ascorbic acid)
Intense Antioxidant Protection Complexion Correction & Age Control
Distributed By:
Skin Beauty Solutions Elk Grove CA 95759
1 oz/30 ml

keep out of reach of children section

INDICATIONS AND USAGE

Perform a patch test before using. Apply 3-5 drops once daily followed by moisturizer. For external use only.

PACKAGE LABEL

Content of labeling